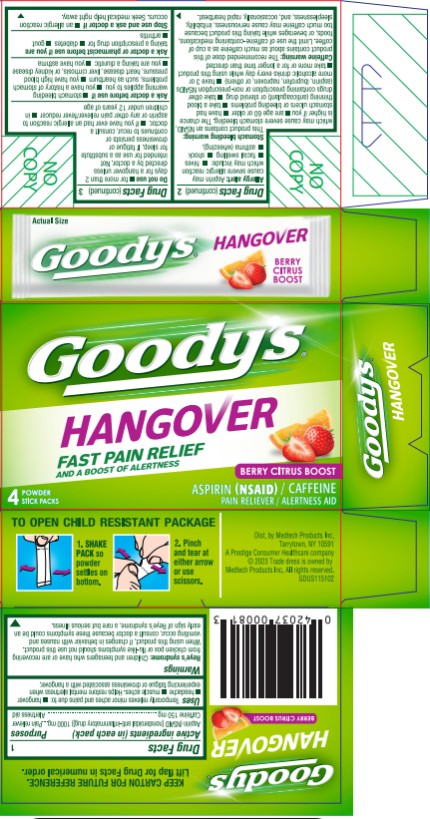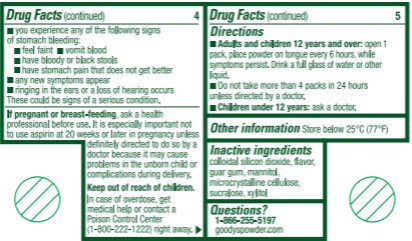 DRUG LABEL: GOODYS
NDC: 63029-665 | Form: POWDER
Manufacturer: Medtech Products Inc.
Category: otc | Type: HUMAN OTC DRUG LABEL
Date: 20251023

ACTIVE INGREDIENTS: CAFFEINE 150 mg/1 1; ASPIRIN 1000 mg/1 1
INACTIVE INGREDIENTS: SILICON DIOXIDE; GUAR GUM; MANNITOL; MICROCRYSTALLINE CELLULOSE; SUCRALOSE; XYLITOL

Goodys Hangover

Drug Facts

Purposes

Aspirin (NSAID*) 1000 mg…………………………………......Pain reliever

Caffeine 150 mg……………………………….…………………Alertness aid

*nonsteroidal anti-inflammatory drug

Uses

Temporarily relieves minor aches and pains due to:

- hangover
- headache
- muscle aches

Helps restore mental alertness when experiencing fatigue or drowsiness associated with a hangover

Warnings

Reye’s syndrome: Children and teenagers who have or are recovering from chicken pox or flu-like symptoms should not use this product. When using this product, if changes in behavior with nausea and vomiting occur, consult a doctor because these symptoms could be an early sign of Reye’s syndrome, a rare but serious illness.

Allergy Alert: Aspirin may cause severe allergic reaction which may include:

• hives • facial swelling • shock • asthma (wheezing).

Stomach bleeding warning: This product contains an NSAID, which may cause severe stomach bleeding. The chance is higher if you

• are age 60 or older

• have had stomach ulcers or bleeding problems

• take a blood thinning (anticoagulant) or steroid drug

• take other drugs containing prescription or non-prescription NSAIDs (aspirin, ibuprofen, naproxen, or others)

• have 3 or more alcoholic drinks every day while using this product

• take more or for a longer time than directed.

Caffeine warning:

The recommended dose of this product contains about as much caffeine as a cup of coffee. Limit the use of caffeine-containing medications, foods, or beverages while taking this product because too much caffeine may cause nervousness, irritability, sleeplessness, and, occasionally, rapid heart beat.

Do not use

▪ for more than 2 days for a hangover unless directed by a doctor. Not intended for use as a substitute for sleep. If fatigue or drowsiness persists or continues to recur, consult a doctor.

▪ if you have ever had an allergic reaction to aspirin or any other pain reliever/fever reducer

▪ in children under 12 years of age

Ask a doctor before use if

• stomach bleeding warning applies to you

• you have a history of stomach problems, such as heartburn

• you have high blood pressure, heart disease, liver cirrhosis, or kidney disease

• you are taking a diuretic

• you have asthma

Ask a doctor or pharmacist before use if you are

taking a prescription drug for ▪ diabetes ▪ gout ▪ arthritis

Stop use and ask a doctor if

• an allergic reaction occurs. Seek medical help right away

• you experience any of the following signs of stomach bleeding

•feel faint • vomit blood • have bloody or black stool

• have stomach pain that does not get better

• any new symptoms appear

• ringing in the ears or a loss of hearing occurs

These could be signs of a serious condition.

If pregnant or breast-feeding,

ask a health professional before use. It is especially important not to use aspirin at 20 weeks or later in pregnancy unless definitely directed to do so by a doctor because it may cause problems in the unborn child or complications during delivery.

Keep out of reach of children.

In case of overdose, get medical help or contact a Poison Control Center (1-800-222-1222) right away.

Directions

•Adults and children 12 years and over: open 1 pack, place powder on tongue every 6 hours, while symptoms persist. Drink a full glass of water or other liquid.

•Do not take more than 4 powders in 24 hours unless directed by a doctor.

•Children under 12 years: ask a doctor.

Other information

Store below 25°C (77°F)

Inactive ingredients

colloidal silicon dioxide, flavor, guar gum, mannitol, microcrystalline cellulose, sucralose, xylitol.

Questions?

1-866-255-5197 goodyspowder.com

PRINCIPAL DISPLAY PANEL

Goody’s® Hangover

Berry Citrus Boost

ASPIRIN (NSAID) / PAIN RELIEVER, CAFFEINE /ALERTNESS AID

4 powder stick packs